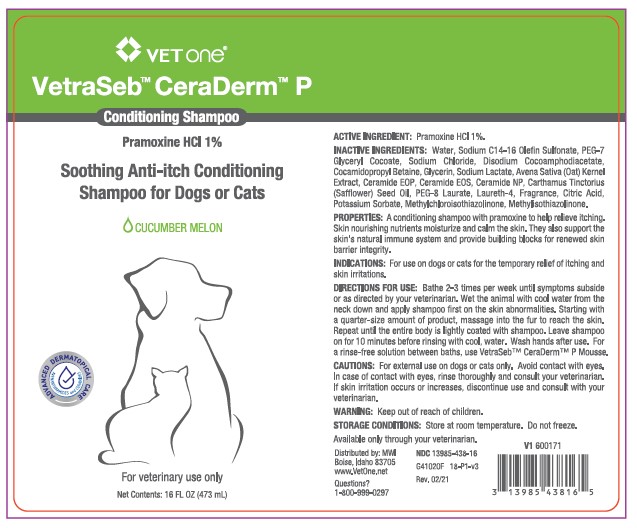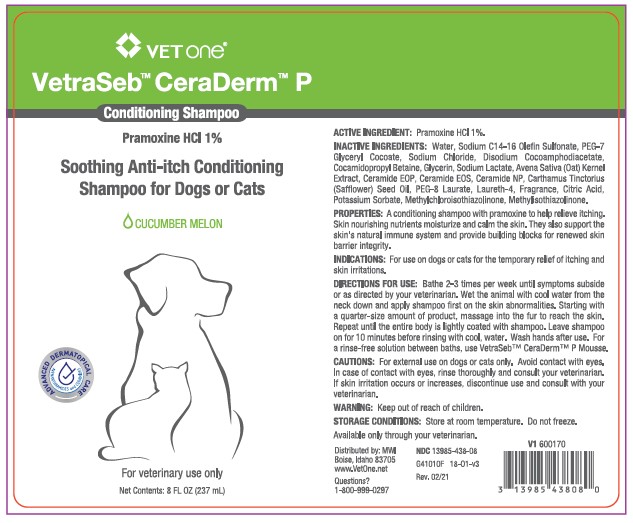 DRUG LABEL: VetraSeb CeraDerm
NDC: 13985-438 | Form: SHAMPOO
Manufacturer: MWI/VETONE
Category: animal | Type: OTC ANIMAL DRUG LABEL
Date: 20210406

ACTIVE INGREDIENTS: PRAMOXINE HYDROCHLORIDE 10 mg/1 mL
INACTIVE INGREDIENTS: WATER; SODIUM C14-16 OLEFIN SULFONATE; PEG-7 GLYCERYL COCOATE; SODIUM CHLORIDE; DISODIUM COCOAMPHODIACETATE; COCAMIDOPROPYL BETAINE; GLYCERIN; SODIUM LACTATE; AVENANTHRAMIDES; CERAMIDE 1; CERAMIDE EOS; CERAMIDE NP; SAFFLOWER OIL; PEG-8 LAURATE; LAURETH-4; CITRIC ACID MONOHYDRATE; POTASSIUM SORBATE; METHYLCHLOROISOTHIAZOLINONE; METHYLISOTHIAZOLINONE

DESCRIPTION

VetraSeb™ CeraDerm™ P

Conditioning Shampoo

Pramoxine HCl 1%

Soothing Ant-itch Conditioning Shampoo for Dogs or Cats

CUCUMBER MELON

ACTIVE INGREDIENTS: Pramoxine HCI 1%.

INACTIVE INGREDIENTS: Water, Sodium C14-16 Olefin Sulfonate, PEG-7 Glyceryl Cocoate, Sodium Chloride, Disodium Cocoamphodiacetate, Cocamidopropyl Betaine, Glycerin, Sodium Lactate, Avena Sativa (Oat) Kernal Extract, Ceramide EOP, Ceramide EOS, Ceramide NP, Carthamus Tinctorius (Safflower) Seed Oil, PEG-8, Laurate, Laureth-4, Fragrance, Citric Acid, Potassium Sorbate, Methylchloroisothiazolinone, Methylisothiazolinone.

PROPERTIES: A conditioning shampoo with pramoxine to help relieve itching. Skin nourishing nutrients moisturize and calm the skin. They also support the skin's natural immune system and provide building blocks for renewed skin barrier integrity.

INDICATIONS AND USAGE

INDICATIONS: For use on dogs or cats for the temporary relief of itching and skin irritations.

DIRECTIONS FOR USE: Bathe 2-3 times per week until symptoms subside or as directed by your veterinarian. Wet the animal with cool water from the neck down and apply shampoo first on the skin abnormalities. Starting with a quarter-size amount of product, massage into the fur to reach the skin. Repeat until the entire body is lightly coated with shampoo. Leave shampoo on for 10 minutes before rinsing with cool water. Wash hands after use. For a rinse-free solution between baths, use VetraSeb™ CeraDerm™ P Mousse.

WARNINGS AND PRECAUTIONS

CAUTIONS: For external use on dogs and cats only. Avoid contact with eyes. In case of contact with eyes, rinse thoroughly and consult your veterinarian. If skin irritation occurs or increases, discontinue use and consult with your veterinarian.

WARNING: Keep out of reach of children.

STORAGE AND HANDLING

STORAGE CONDITIONS: Store at room temperature. Do not freeze.

Available only through your veterinarian.

Distributed by: MWI

Boise, Idaho 83705

www.VetOne.net

QUESTIONS?

1-800-999-0297

PRINCIPAL DISPLAY PANEL - 8 OUNCE (237 mL) Bottle

VetOne®

VetraSeb™ CeraDerm™ P

Conditioning Shampoo

Pramoxine HCl 1%

Soothing Anti-itch Conditioning Shampoo for Dogs or Cats

CUCUMBER MELON

For veterinary use only

Net Contents: 8 FL. OZ. (237 mL)

PRINCIPAL DISPLAY PANEL - 16 OUNCE (473 mL) Bottle

VetOne®

VetraSeb™ CeraDerm™ P

Conditioning Shampoo

Pramoxine HCl 1%

Soothing Anti-itch Conditioning Shampoo for Dogs or Cats

CUCUMBER MELON

For veterinary use only

Net Contents: 16 FL. OZ. (473 mL)